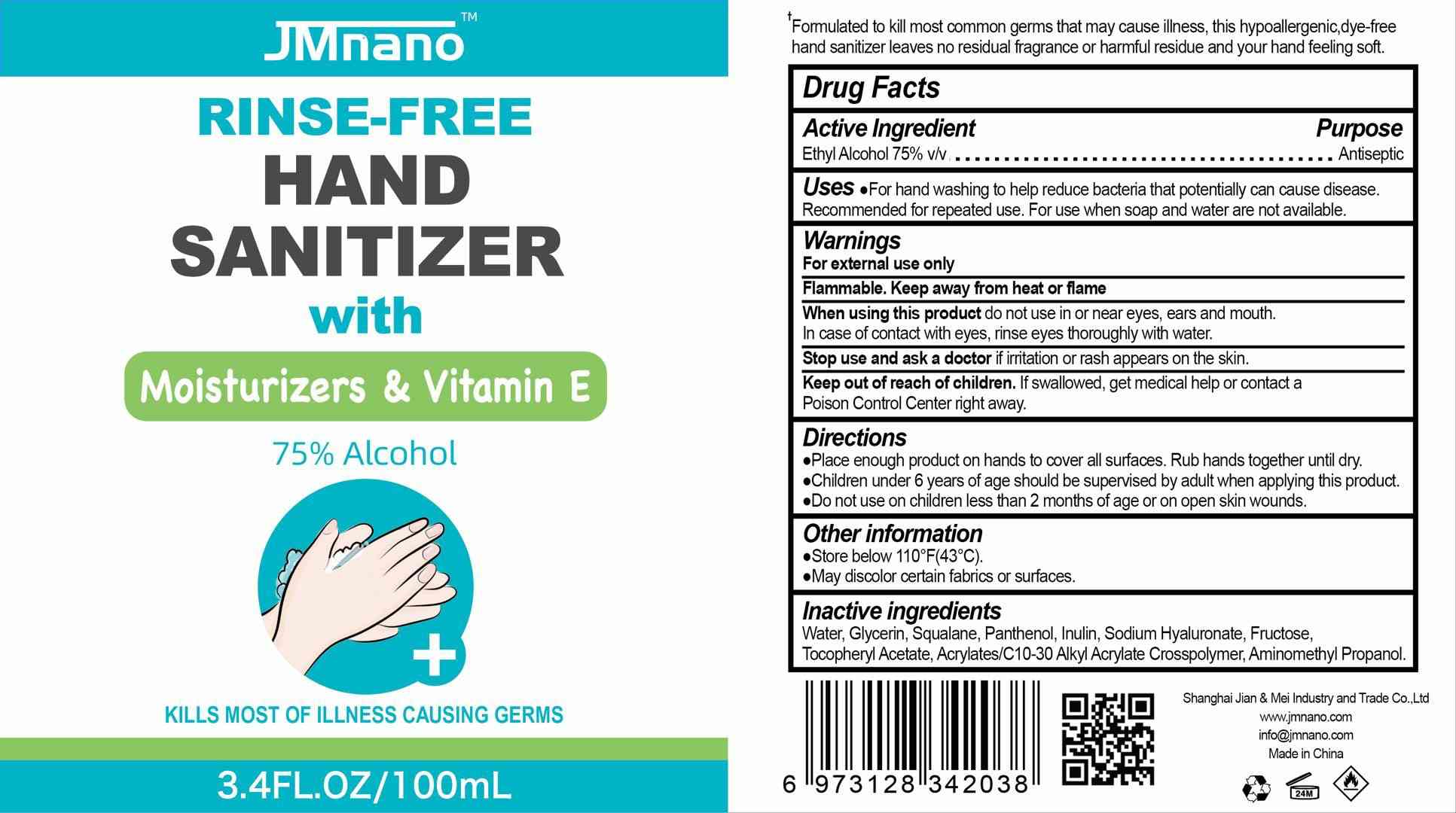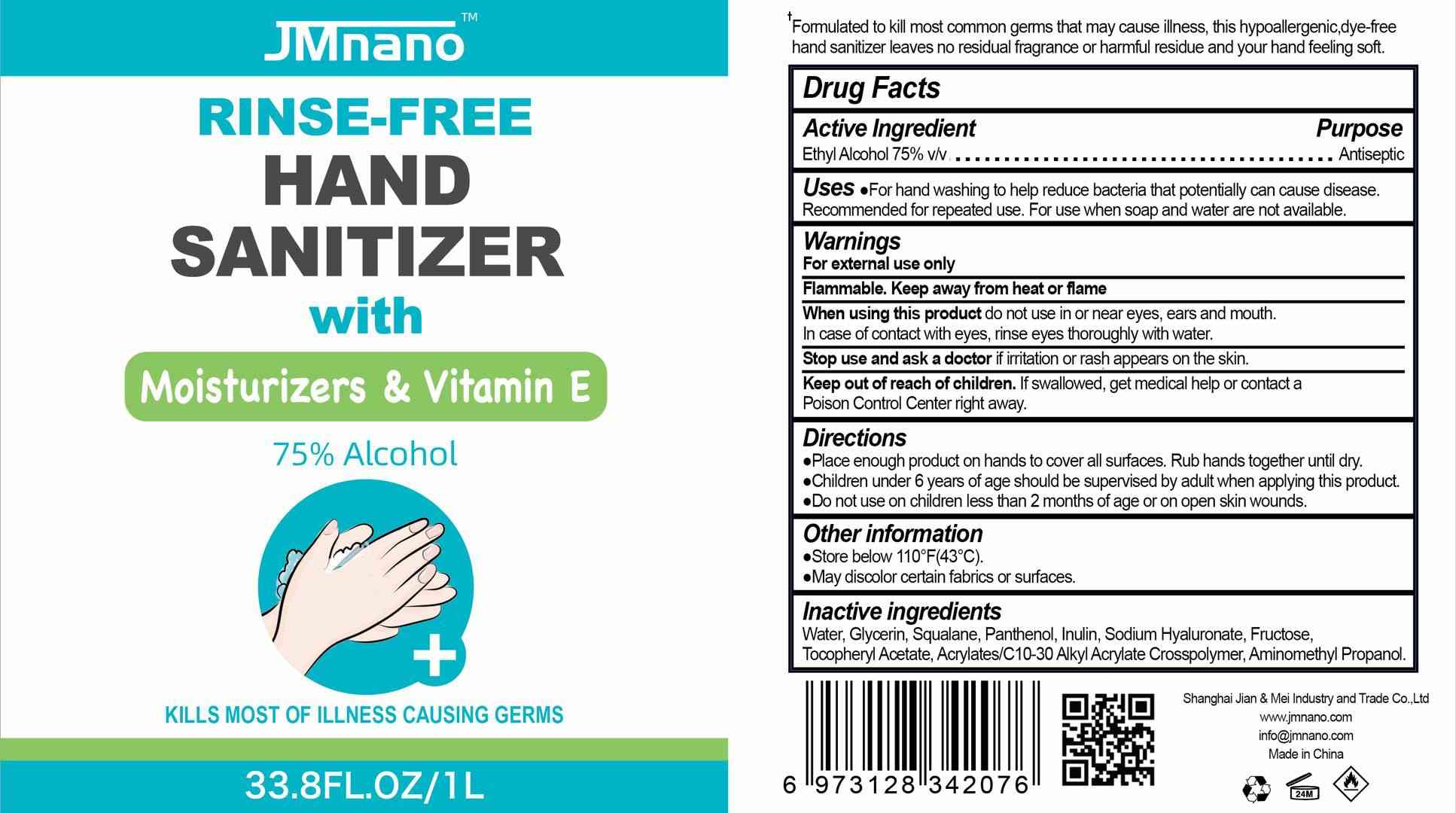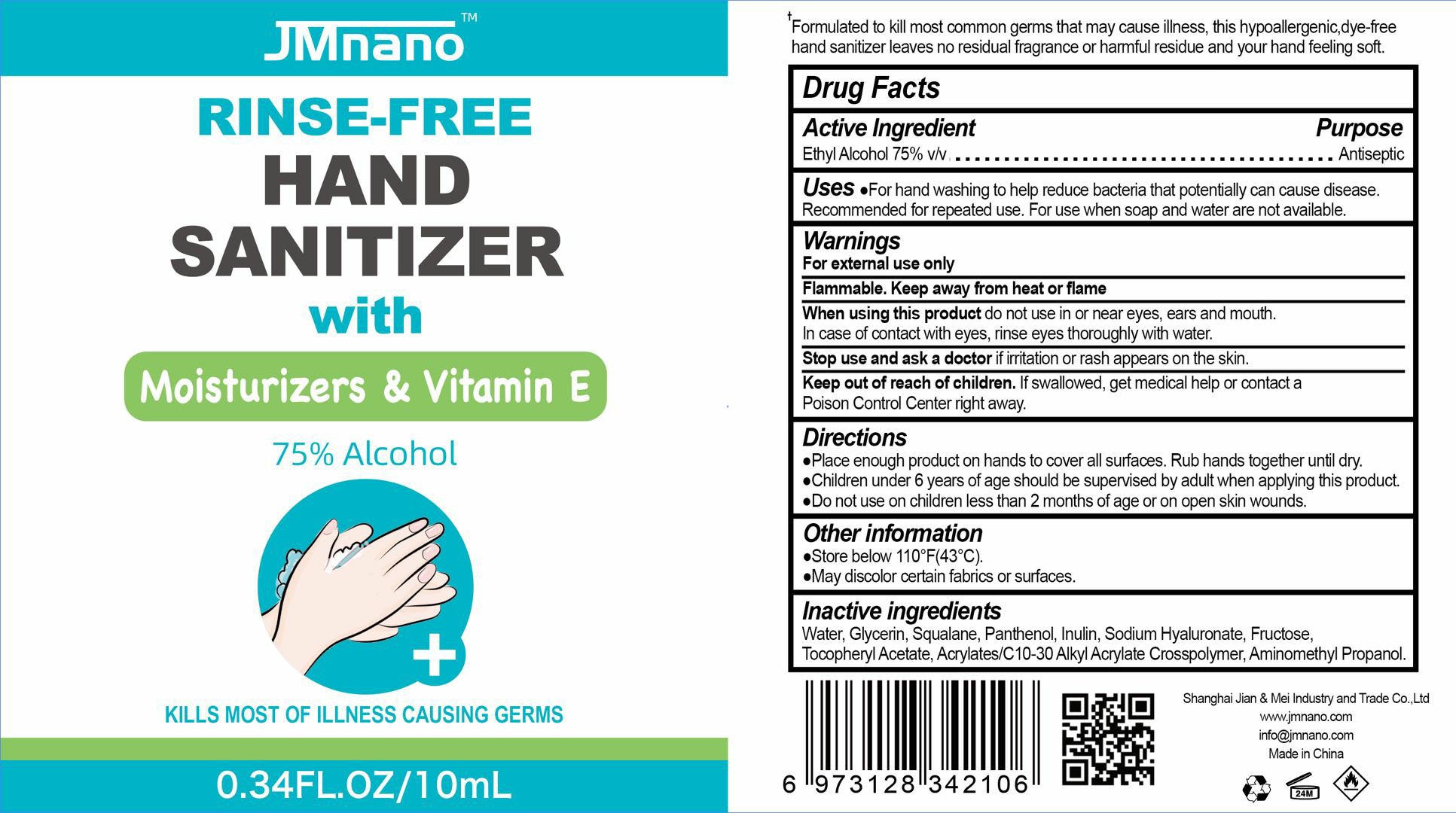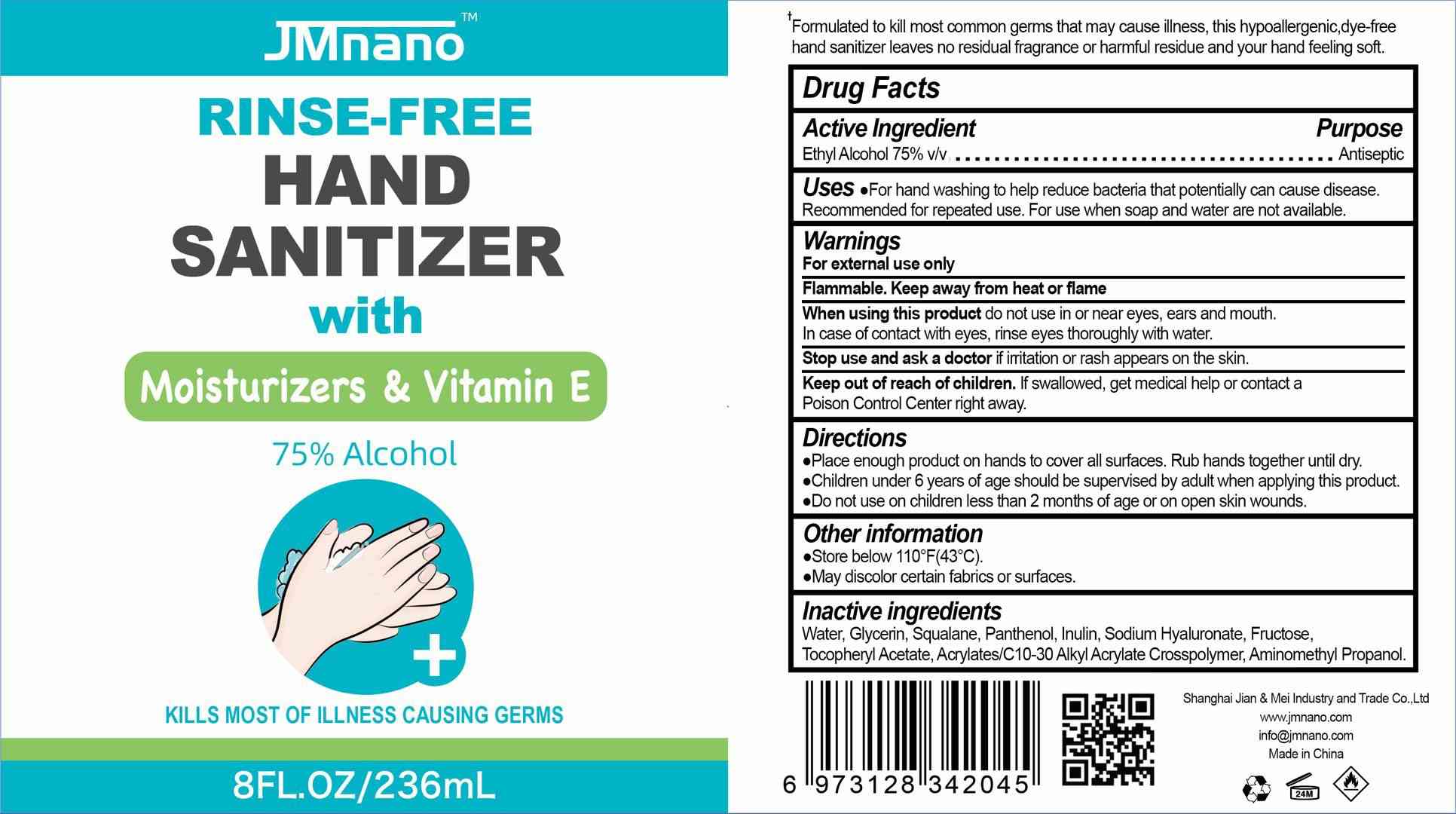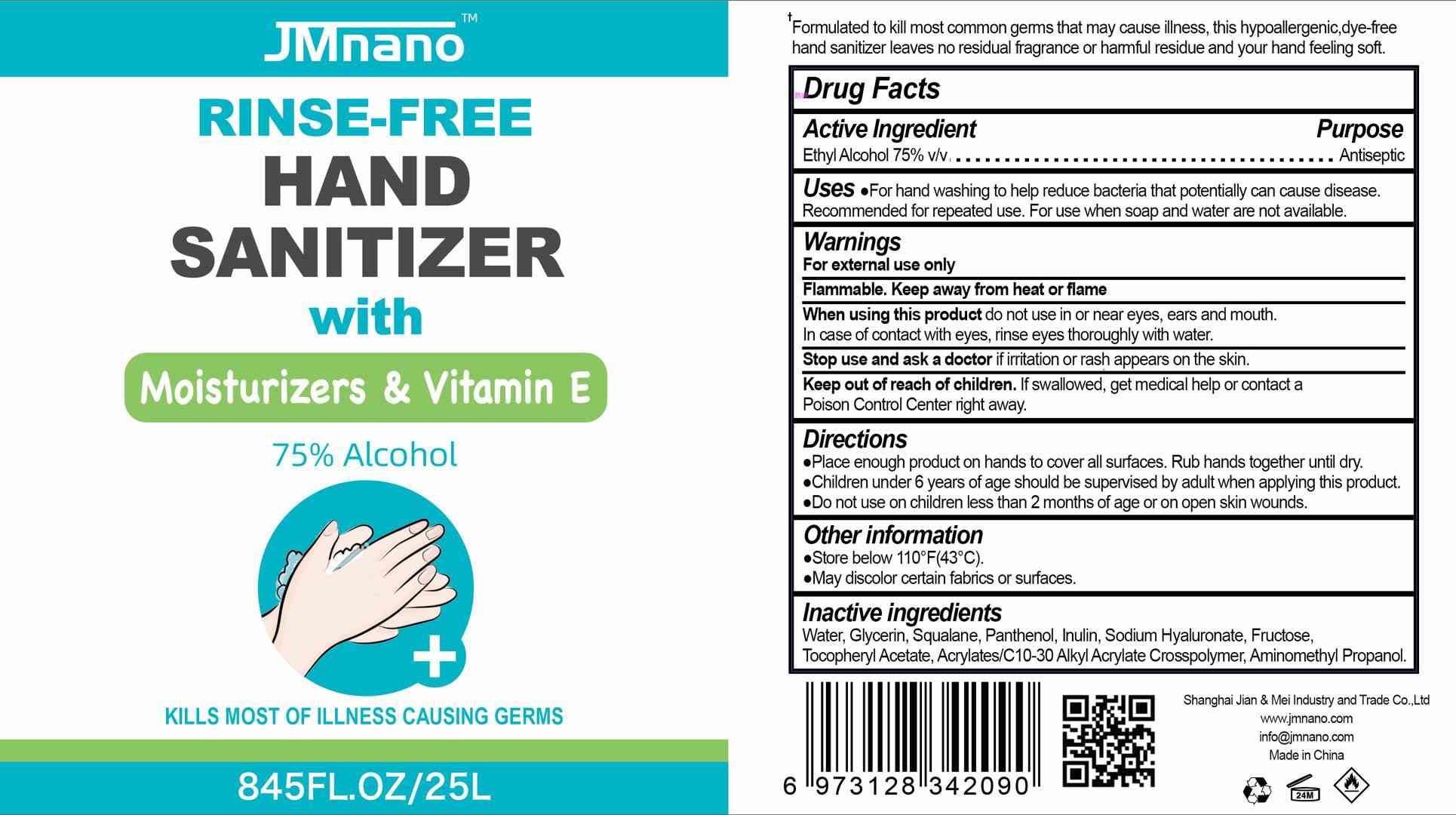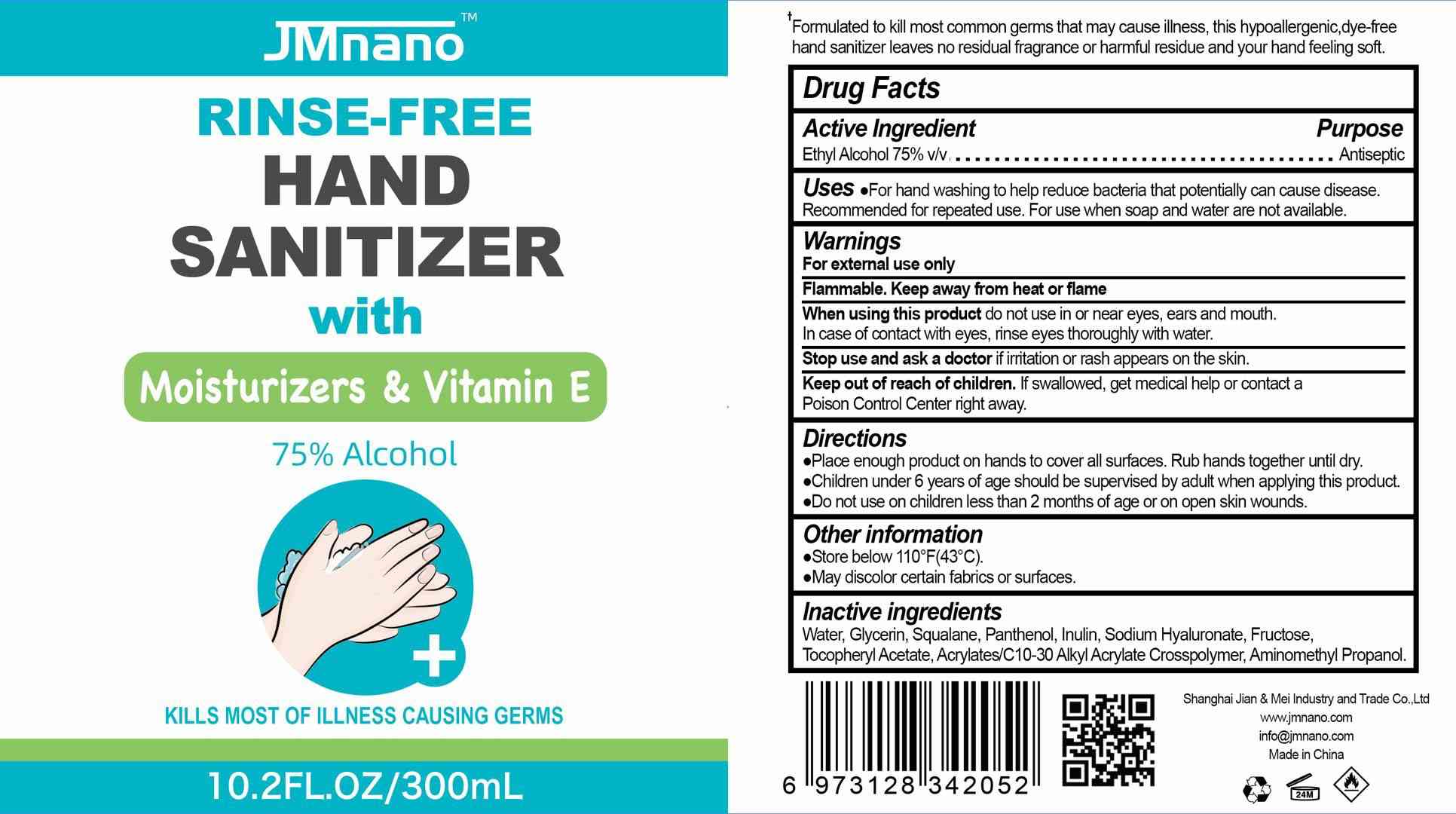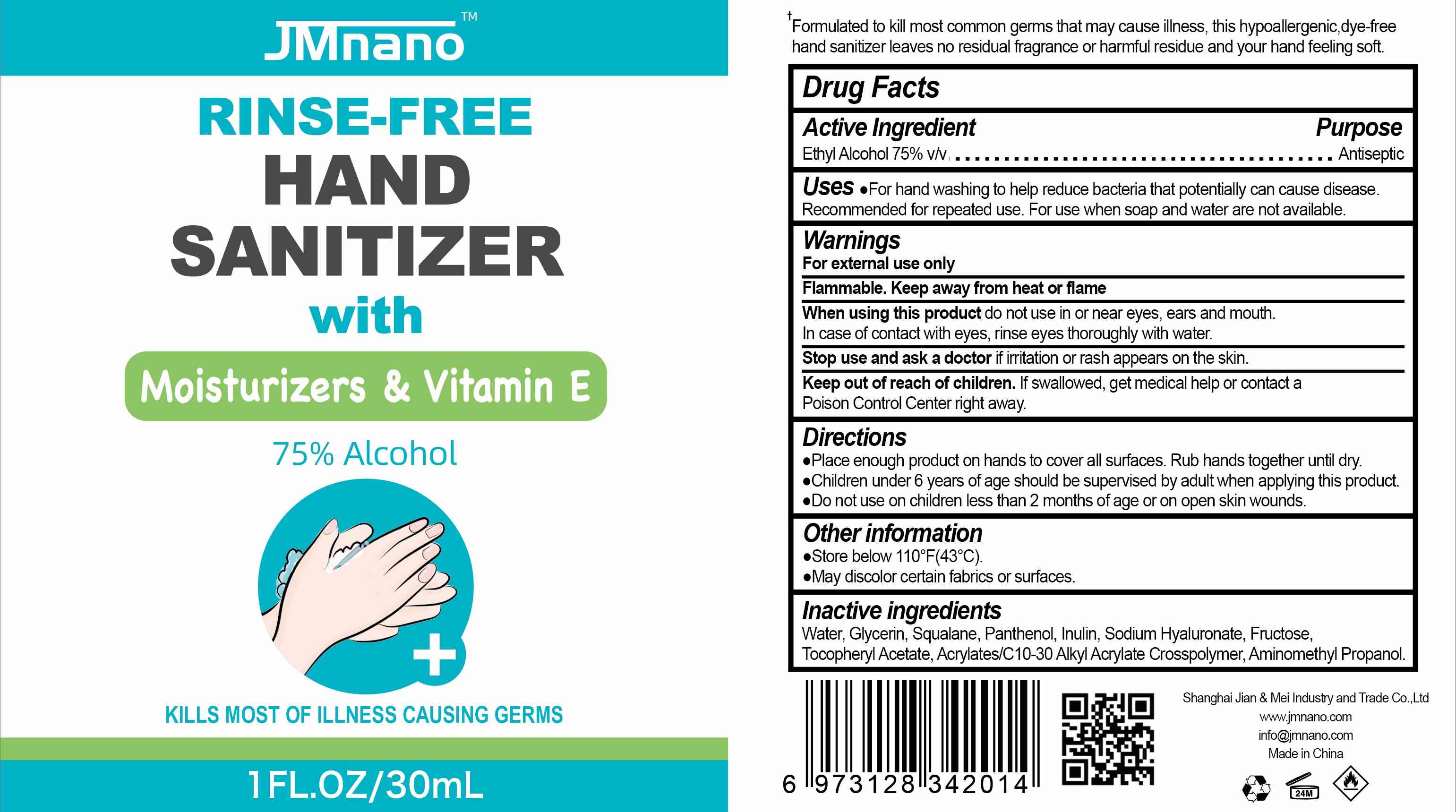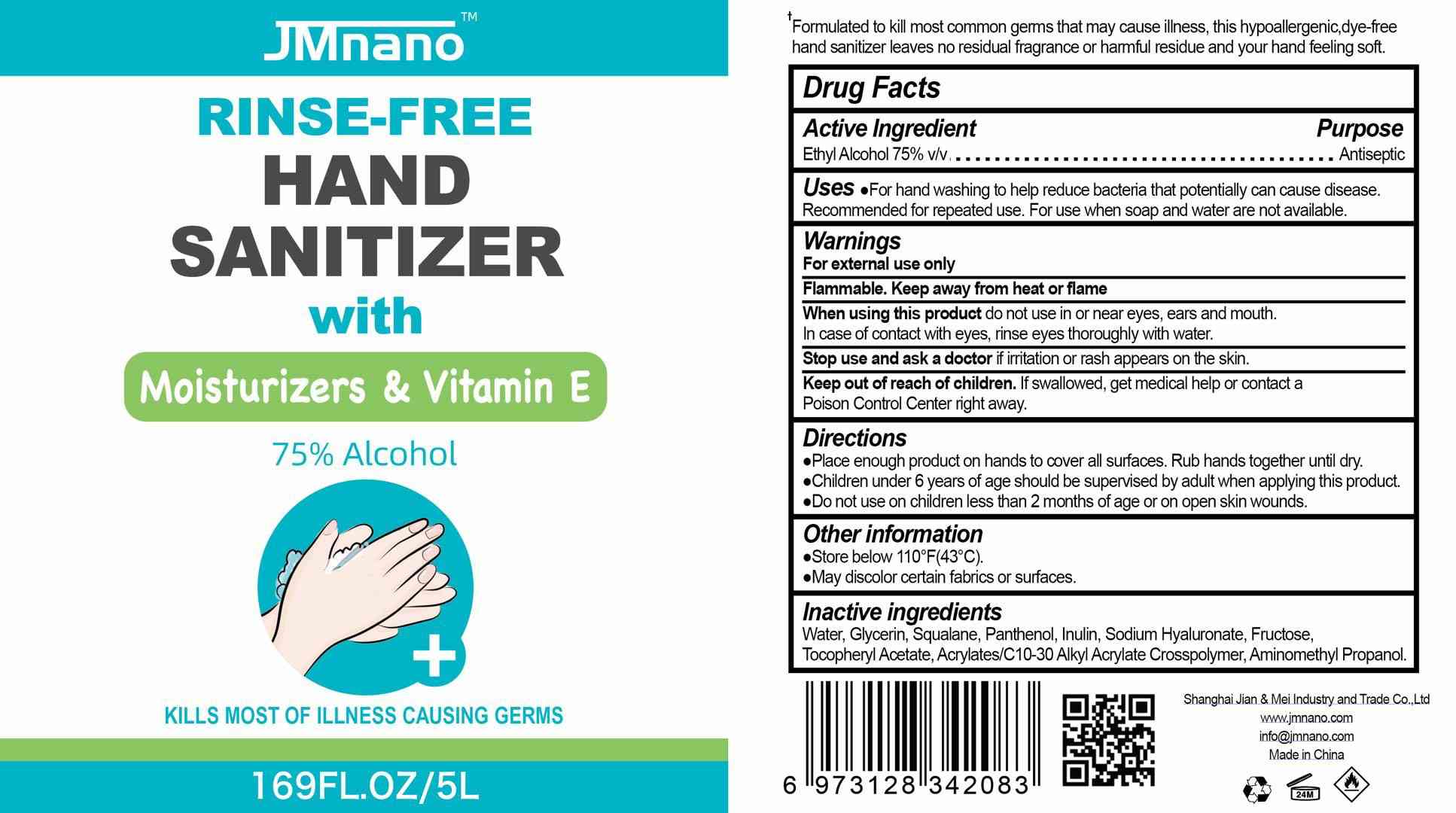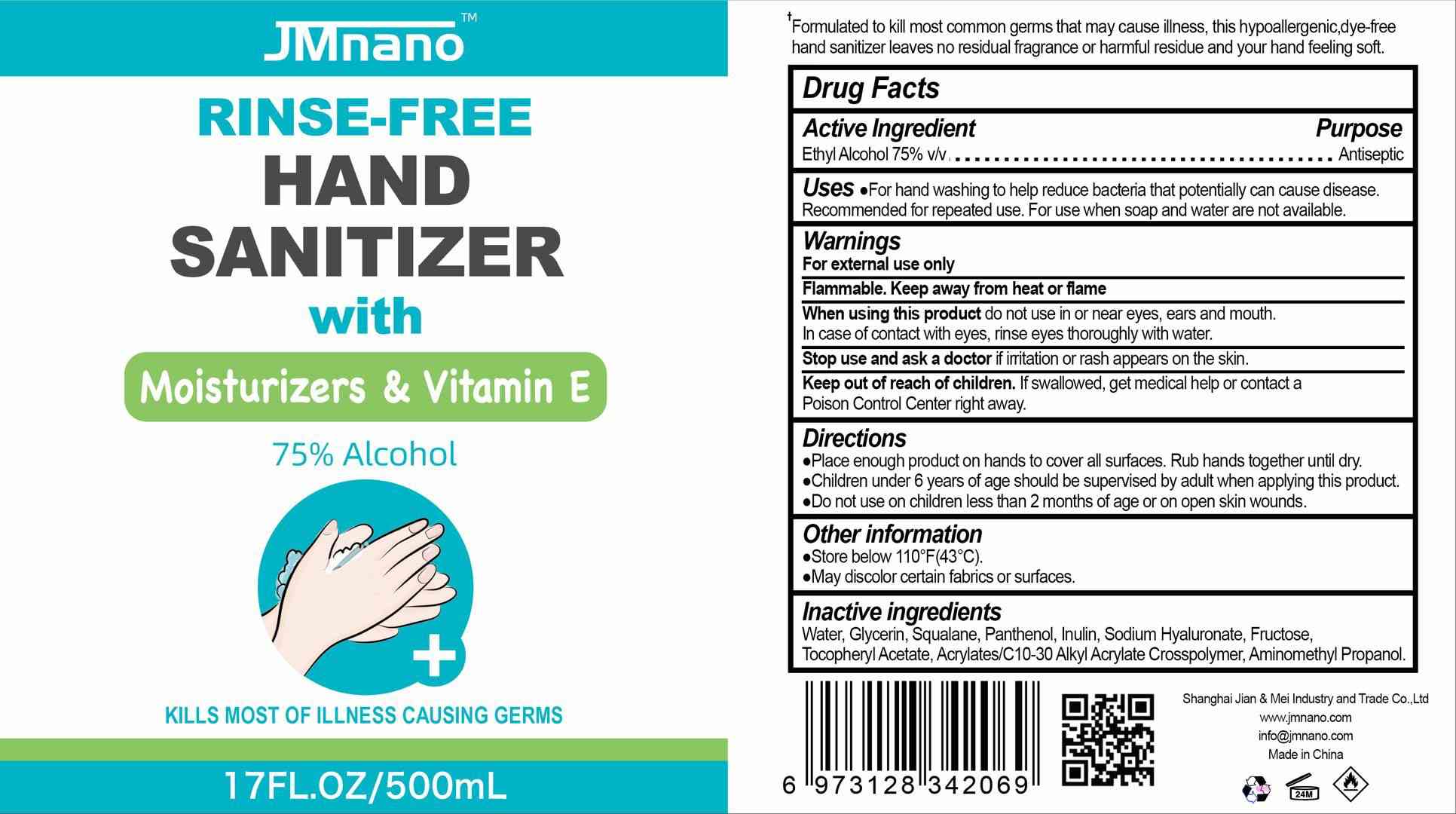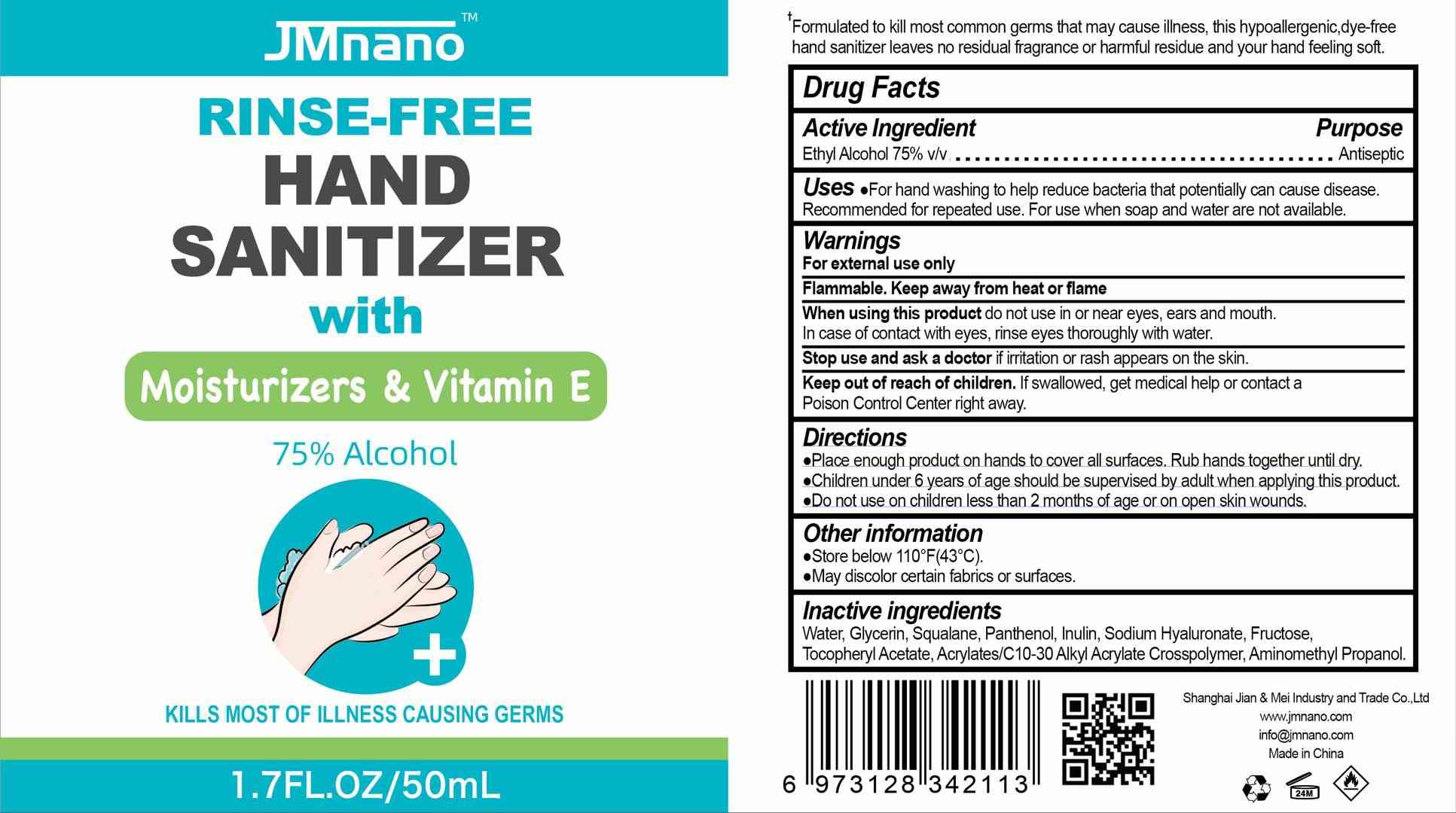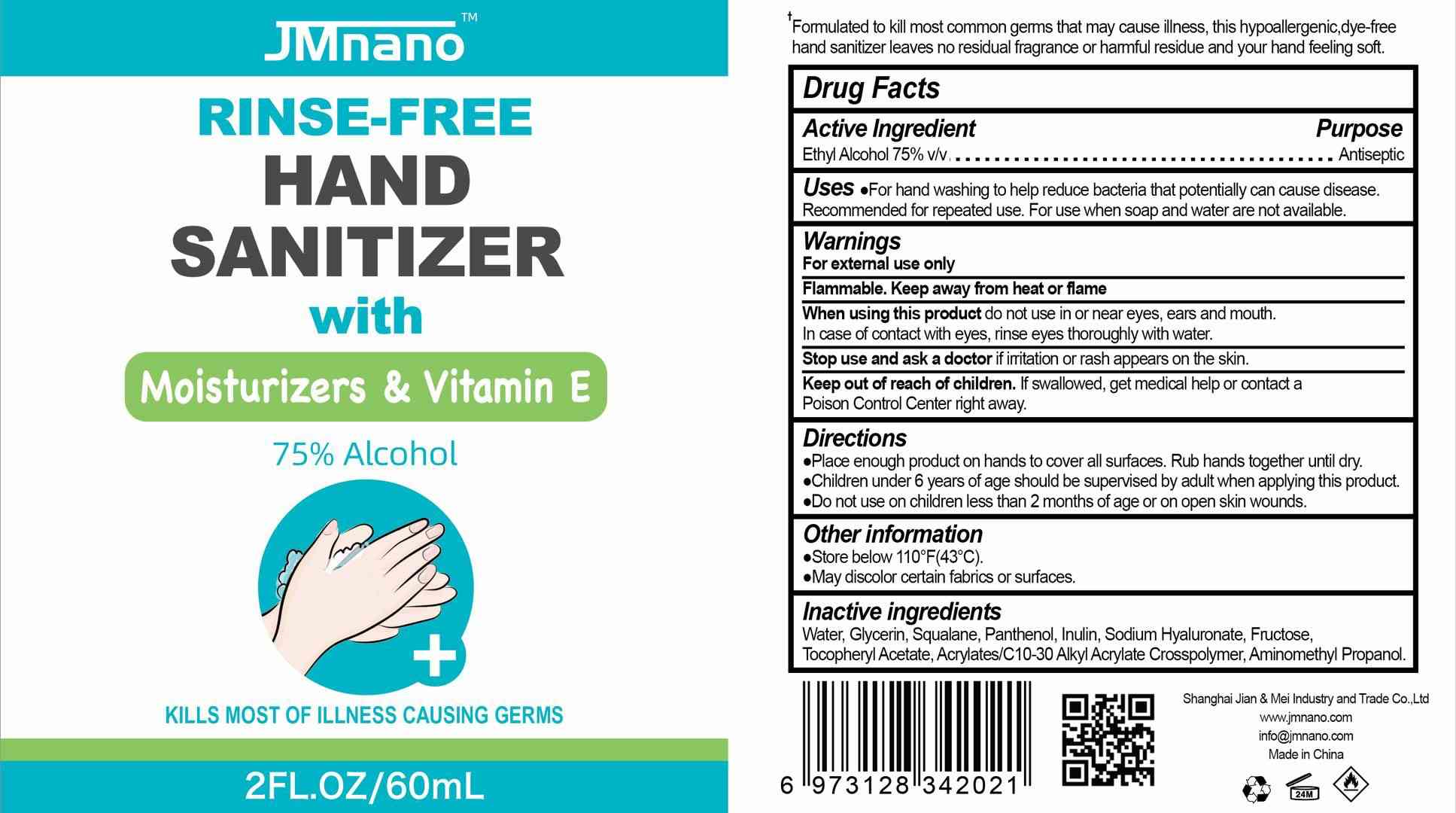 DRUG LABEL: JMnano  Rinse-free  Hand Sanitizer
NDC: 76631-007 | Form: GEL
Manufacturer: Shanghai Jian & Mei Industry and Trade Co.,Ltd
Category: otc | Type: HUMAN OTC DRUG LABEL
Date: 20200526

ACTIVE INGREDIENTS: ALCOHOL 75 mL/100 mL
INACTIVE INGREDIENTS: AMINOMETHYLPROPANOL; WATER; HYALURONATE SODIUM; .ALPHA.-TOCOPHEROL ACETATE; SQUALANE; INULIN; GLYCERIN; PANTHENOL; FRUCTOSE; CARBOMER INTERPOLYMER TYPE A (ALLYL SUCROSE CROSSLINKED)

JMnano Rinse-free Hand Sanitizer

ACTIVE INGREDIENTS

Ethyl Alcohol 75%v/v

PURPOSE

Antiseptic

INACTIVE INGREDIENT(S)

Water, Glycerin, Squalane, Panthenol, Inulin, Sodium Hyaluronate, Fructose,Tocopheryl Acetate, Acrylates/C10-30 Alkyl Acrylate Crosspolymer, Aminomethyl Propanol

WARNINGS

For external use only

Flammable. Keep away from heat or flame

OTHER INFORMATION

store below 110F(43℃)
May discolor certain fabrics or surfaces.

do not use

When using this product do not use in or near eyes, ears and mouth.

When using this product do not use in or near eyes, ears and mouth.
In case of contact with eyes, rinse eyes thoroughly with water.

Stop use and ask a doctor if irritation or rash appears on the skin.

Keep out of reach of children. If swallowed, get medical help or contact a Poison Control Center right away.

Directionso

Place enough product on hands to cover all surfaces. Rub hands together until dry.
Children under 6 years of age should be supervised by adult when applying this product.
Do not use on children less than 2 months of age or on open skin wounds.

INDICATIONS AND USAGE

Uses .For hand washing to help reduce bacteria that potentially can cause disease!Recommended for repeated use. For use when soap and water are not available

DOSAGE AND ADMINISTRATION

、